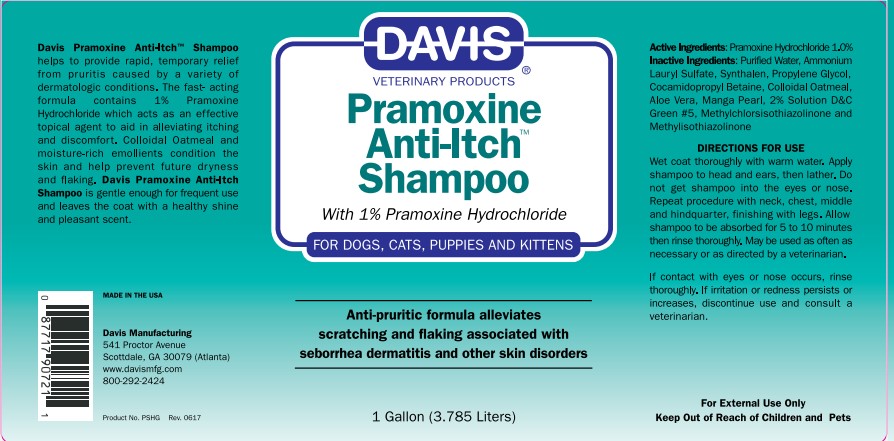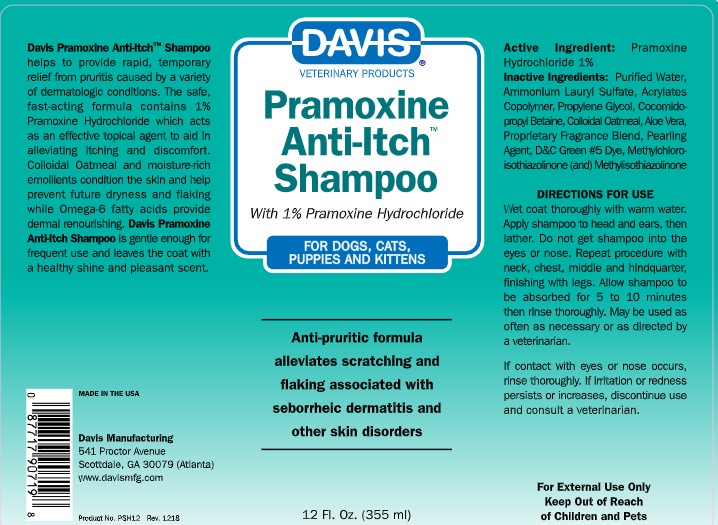 DRUG LABEL: Pramoxine Anti Itch
NDC: 62570-101 | Form: SHAMPOO
Manufacturer: Davis Manufacturing and Packaging Inc
Category: animal | Type: OTC ANIMAL DRUG LABEL
Date: 20191106

ACTIVE INGREDIENTS: PRAMOXINE HYDROCHLORIDE 1 g/100 g
INACTIVE INGREDIENTS: WATER; METHACRYLIC ACID - ETHYL ACRYLATE COPOLYMER (1:1) TYPE A; AMMONIUM LAURYL SULFATE; PROPYLENE GLYCOL; COCAMIDOPROPYL BETAINE; OATMEAL; ALOE VERA LEAF; FD&C YELLOW NO. 5; METHYLCHLOROISOTHIAZOLINONE/METHYLISOTHIAZOLINONE MIXTURE

Pramoxine Anti-Itch Shampoo

DESCRIPTION

Davis Pramoxine Anti-ItchTM Shampoo helps to provide rapid, temporary relief from pruritis caused by a variety of dermatologic conditions. The safe, fast acting formula contains 1% Pramoxine Hydrochloride which acts as an effective topical agent to aid in alleviating itching and discomfort. Colloidal Oatmeal and moisture-rich emollients condition the skin and help prevent future dryness and flaking while Omega-6 fatty acids provide dermal nourishing. Davis Pramoxine Anti-Itch Shampoo is gentle enough for frequent use and leaves the coat with a healthy shine and pleasant scent.

Environment Friendly

MADE IN THE USA

Davis Manufacturing

541 Proctor Avenue

Atlanta/Scottdale, GA 30079

www.davismfg.com

800-292-2424

Active Ingredients: Pramoxine Hydrochloride 1.0%

INACTIVE INGREDIENT

Inactive Ingredients: Purified Water, Cetyl Alcohol, Cetearyl Alcohol & Ceterimenium Bromide, Modified Acrylic Polymer, Germaben II, Cationic Guar Gum, Colloidal Oatmeal, Triethenolamine, Herbal Fragrance, FD&C Yellow #5, Chocolate Dye

DIRECTIONS FOR USE

Wet coat thoroughly with warm water. Apply shampoo to head ears, then lather. Do not get shampoo into eyes or nose. Repeat procedure with neck, chest, middle and hindquarters, finishing with legs. Allow shampoo to be absorbed for 5 to 10 minutes then rinse thoroughly. May be used as often as necessary or as directed by a veterinarian. For optimal results, use in conjunction with Davis Pramoxine Anti-Itch TM Creme Rinse. For added benefit between baths, apply Pramoxine Anti-Itch TM Spray to localized areas.

PRECAUTIONS

If contact with eyes or nose occurs, rinse thoroughly. If irritation or redness persist or increases, discontinue use and consult a veterinarian.

KEEP OUT OF REACH OF CHILDREN

For External Use Only

Keep Out of Reach of Children

PACKAGE LABEL

Davis Veterinary Products
Pramoxine Anti-Itch TM Shampoo
With 1% Pramoxine Hydrochloride
For Dogs, Cats, Puppies and Kittens
Anti-pruritic formula alleviates scratching and flaking associated with seborrhea dermatitis and other skin disorders

12 Fl. Oz. (355 ml)

PACKAGE LABEL

Davis

Veterinary Products

Pramoxine

Anti-Itch TM

Shampoo

With 1% Pramoxine Hydrochloride

For Dogs, Cats, Puppies and Kittens

Anti-pruritic formula alleviates

scratching and flaking associated with

seborrhea dermititis and other skin disorders

1 Gallon (3.785 Liters)